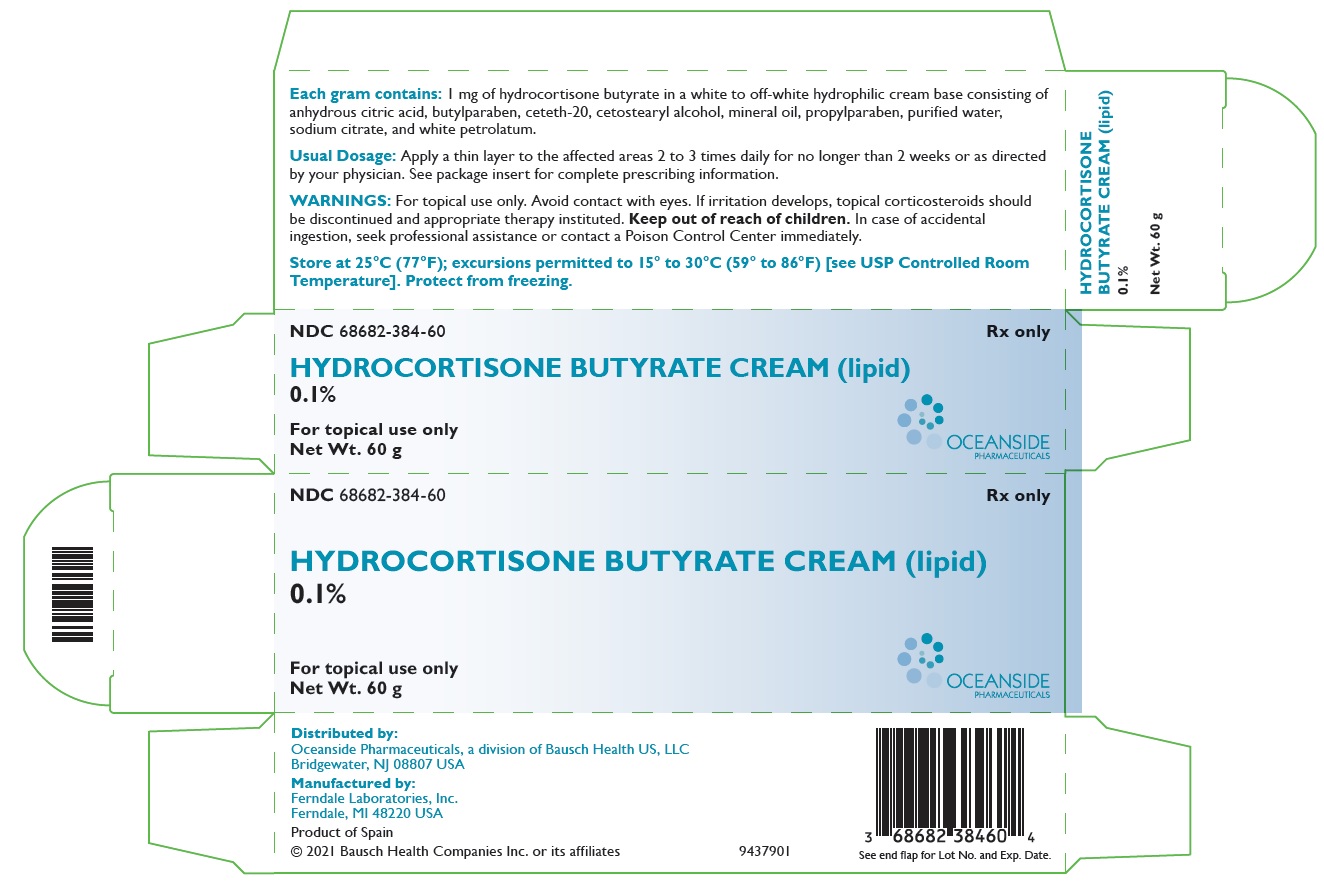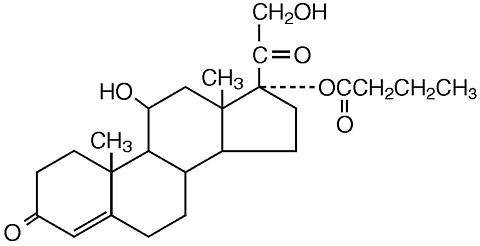 DRUG LABEL: Hydrocortisone Butyrate
NDC: 68682-384 | Form: CREAM
Manufacturer: Oceanside Pharmaceuticals
Category: prescription | Type: HUMAN PRESCRIPTION DRUG LABEL
Date: 20250605

ACTIVE INGREDIENTS: HYDROCORTISONE BUTYRATE 1 mg/1 g
INACTIVE INGREDIENTS: CITRIC ACID MONOHYDRATE; CETETH-20; CETOSTEARYL ALCOHOL; BUTYLPARABEN; MINERAL OIL; PROPYLPARABEN; WATER; SODIUM CITRATE, UNSPECIFIED FORM; PETROLATUM

HIGHLIGHTS OF PRESCRIBING INFORMATION

These highlights do not include all the information needed to use HYDROCORTISONE BUTYRATE CREAM (lipid), 0.1% safely and effectively. See full prescribing information for HYDROCORTISONE BUTYRATE CREAM (lipid), 0.1%.
HYDROCORTISONE BUTYRATE cream (lipid), 0.1%, for topical use
Initial U.S. Approval: 1982

RECENT MAJOR CHANGES

Warnings and Precautions (5.1, 5.2) 7/2024

1 INDICATIONS AND USAGE

Hydrocortisone Butyrate Cream (lipid), 0.1% is a corticosteroid indicated for:

- Relief of the inflammatory and pruritic manifestations of corticosteroid-responsive dermatoses in adults. (1)
- The topical treatment of mild to moderate atopic dermatitis in pediatric patients 3 months of age and older. (1)

2 DOSAGE AND ADMINISTRATION

- Corticosteroid-Responsive Dermatoses:Apply a thin layer to the affected skin areas 2 or 3 times daily for corticosteroid-responsive dermatoses in adults. Rub in gently. (2)
- Atopic Dermatitis:Apply a thin layer to the affected skin areas 2 times daily for atopic dermatitis in pediatric patients 3 months of age and older. Rub in gently. (2)
- Discontinue Hydrocortisone Butyrate Cream (lipid), 0.1% when control is achieved. (2)
- Reassess diagnosis if no improvement is seen within 2 weeks. Before prescribing for more than 2 weeks, weigh any additional benefits of extending treatment up to 4 weeks against the risk of hypothalamic-pituitary-adrenal (HPA) axis suppression and local adverse reactions. (2)
- Avoid use under occlusion or in the diaper area. (2)
- Hydrocortisone Butyrate Cream (lipid), 0.1% is not for oral, ophthalmic, or intravaginal use. (2)

3 DOSAGE FORMS AND STRENGTHS

Cream, 0.1% (1 mg/g). (3)

4 CONTRAINDICATIONS

None. (4)

5 WARNINGS AND PRECAUTIONS

- Endocrine System Adverse Reactions:
- Reversible hypothalamic-pituitary-adrenal (HPA) axis suppression may occur, with the potential for glucocorticosteroid insufficiency. Consider periodic evaluations for HPA-axis suppression if Hydrocortisone Butyrate Cream (lipid), 0.1% is applied to large surface areas or used under occlusion. If HPA-axis suppression is noted, reduce the application frequency, discontinue use, or switch to a lower potency corticosteroid. (5.1, 8.4)
- Systemic effects of topical corticosteroids may also include manifestations of Cushing’s syndrome, hyperglycemia, and glucosuria. (5.1, 8.4)
- Pediatric patients may be more susceptible to systemic toxicity due to their larger skin-surface-to-body-mass ratios. (5.1, 8.4)
- Ophthalmic Adverse Reactions:Topical corticosteroids, including Hydrocortisone Butyrate Cream (lipid), 0.1%, may increase the risk of cataracts and glaucoma. If visual symptoms occur, consider referral to an ophthalmologist. (5.2)
- Skin Infections:Initiate appropriate therapy if concomitant skin infections develop. (5.3)

6 ADVERSE REACTIONS

The most common adverse reactions (≥1%) are application site reactions. (6)

To report SUSPECTED ADVERSE REACTIONS, contact Oceanside Pharmaceuticals at 1-800-321-4576 or FDA at 1-800-FDA-1088 or www.fda.gov/medwatch.

FULL PRESCRIBING INFORMATION

1 INDICATIONS AND USAGE

Hydrocortisone Butyrate Cream (lipid), 0.1% is indicated for:

- Relief of the inflammatory and pruritic manifestations of corticosteroid-responsive dermatoses in adults.
- The topical treatment of mild to moderate atopic dermatitis in pediatric patients 3 months of age and older.

2 DOSAGE AND ADMINISTRATION

Recommended Dosage for Corticosteroid-Responsive Dermatoses

For corticosteroid-responsive dermatoses in adults, apply a thin layer to the affected skin areas 2 or 3 times daily, depending on the severity of the condition, and rub in gently.

Recommended Dosage for Atopic Dermatitis

For atopic dermatitis in patients 3 months of age and older, apply a thin layer to the affected skin areas 2 times daily and rub in gently.

Administration Instructions

- Discontinue therapy when control is achieved.
- If no improvement is seen within 2 weeks, reassessment of the diagnosis may be necessary. Before prescribing for more than 2 weeks, weigh any additional benefits of extending treatment to 4 weeks against the risk of HPA-axis suppression and local adverse events [see Warnings and Precautions(5.1)] .
- Hydrocortisone Butyrate Cream (lipid), 0.1% is not for oral, ophthalmic, or intravaginal use.
- Do not use Hydrocortisone Butyrate Cream (lipid), 0.1%:
- With occlusive dressings unless directed by a healthcare provider. Avoid use in the diaper area, as diapers or plastic pants may constitute occlusive dressings.
- On the face, underarms, or groin areas unless directed by a healthcare provider.

3 DOSAGE FORMS AND STRENGTHS

Cream: Each gram contains 1 mg of hydrocortisone butyrate (0.1%) in a white to off-white hydrophilic cream base.

4 CONTRAINDICATIONS

None.

5 WARNINGS AND PRECAUTIONS

5.1 Endocrine System Adverse Reactions

Hypothalamic-Pituitary-Adrenal (HPA) Axis Suppression

Use of topical corticosteroids, including Hydrocortisone Butyrate Cream (lipid), 0.1%, can cause systemic adverse reactions including HPA-axis suppression with the potential for clinical glucocorticosteroid insufficiency. Factors that predispose a patient to HPA axis suppression include the use of high-potency steroids, large treatment surface areas, prolonged use, use of occlusive dressings, altered skin barrier, liver failure, and young age. Consider patients for periodic evaluation of the HPA axis. This may be done by using cosyntropin (ACTH1-24) stimulation testing (CST). If HPA-axis suppression is noted, reduce the frequency of application or withdraw Hydrocortisone Butyrate Cream (lipid), 0.1%, or substitute a less potent corticosteroid. Signs and symptoms of glucocorticosteroid insufficiency may occur, requiring supplemental systemic corticosteroids.

Studies conducted in pediatric subjects demonstrated reversible HPA-axis suppression after use of Hydrocortisone Butyrate Cream (lipid), 0.1%. Pediatric patients may be more susceptible than adults to systemic toxicity from equivalent doses of Hydrocortisone Butyrate Cream (lipid), 0.1% due to their larger skin-surface-to-body-mass ratios [ see Use in Specific Populations (8.4) , Clinical Pharmacology (12.2) ].

Cushing’s Syndrome, Hyperglycemia, and Glucosuria

Systemic adverse reactions of topical corticosteroids, including Hydrocortisone Butyrate Cream (lipid), 0.1%, may also include manifestations of Cushing’s syndrome, hyperglycemia, and glucosuria.

Additional Considerations for Endocrine Adverse Reactions

Use of more than one corticosteroid-containing product at the same time may increase total systemic corticosteroid exposure.

Minimize systemic corticosteroid effects by mitigating the risk factors for increased systemic absorption and using Hydrocortisone Butyrate Cream (lipid), 0.1% as recommended [ see Dosage and Administration (2) ].

5.2 Ophthalmic Adverse Reactions

Use of topical corticosteroids, including Hydrocortisone Butyrate Cream (lipid), 0.1%, may increase the risk of posterior subcapsular cataracts and glaucoma. Cataracts and glaucoma have been reported in postmarketing experience with the use of topical corticosteroid products [ see Adverse Reactions (6.2) ].

Avoid contact of Hydrocortisone Butyrate Cream (lipid), 0.1% with eyes. Advise patients to report any visual symptoms and consider referral to an ophthalmologist for evaluation.

5.3 Skin Infections

Use of topical corticosteroids, including Hydrocortisone Butyrate Cream (lipid), 0.1%, may delay healing or worsen concomitant skin infections. If skin infections are present or develop, use an appropriate antifungal, antibacterial or antiviral agent. If a favorable response does not occur promptly, discontinue use of Hydrocortisone Butyrate Cream (lipid), 0.1% until the infection has been adequately controlled.

5.4 Allergic Contact Dermatitis

Use of topical corticosteroids, including Hydrocortisone Butyrate Cream (lipid), 0.1%, can cause allergic contact dermatitis Allergic contact dermatitis with corticosteroids is usually diagnosed by observing a failure to heal rather than noticing a clinical exacerbation. Such an observation should be corroborated with appropriate patch testing. Discontinue Hydrocortisone Butyrate Cream (lipid), 0.1% if the diagnosis is established.

6 ADVERSE REACTIONS

The following adverse reactions are discussed in greater detail in other sections of the labeling:

- Endocrine system adverse reactions [see Warnings and Precautions (5.1), Use in Specific Populations (8.4)]
- Ophthalmic adverse reactions [see Warnings and Precautions (5.2)]
- Skin infections [see Warnings and Precautions (5.3)]
- Allergic contact dermatitis [see Warnings and Precautions (5.4)]

6.1 Clinical Trials Experience

Because clinical trials are conducted under widely varying conditions, adverse reaction rates observed in the clinical trials of a drug cannot be directly compared to rates in the clinical trials of another drug and may not reflect the rates observed in clinical practice.

The safety data derived from Hydrocortisone Butyrate Cream (lipid), 0.1% clinical trials reflect exposure to Hydrocortisone Butyrate Cream (lipid), 0.1% twice daily for up to 4 weeks in pediatric subjects 3 months of age and older with mild to moderate atopic dermatitis.

Table 1. Frequency of Adverse Reactions in Pediatric Subjects 3 Months of Age and Older with Mild to Moderate Atopic Dermatitis
 | Hydrocortisone Butyrate Cream (lipid), 0.1% (n=131) | Vehicle (n=133)
Application site folliculitis | 1% | 0.0%
Application site irritation | 1% | 0.0%
Acne | 1% | 0.0%

6.2 Postmarketing Experience

The following adverse reactions have been reported during post approval use of topical corticosteroids, including Hydrocortisone Butyrate Cream (lipid), 0.1%. Because these reactions are reported voluntarily from a population of uncertain size, it is not always possible to reliably estimate their frequency or establish a causal relationship to drug exposure.

Local Adverse Reactions:burning, itching, drying, hypertrichosis, acneiform eruptions, hypopigmentation, perioral dermatitis, allergic contact dermatitis, maceration of the skin, secondary infection, skin atrophy, striae, and miliaria.

Ophthalmic Adverse Reactions: blurred vision, cataracts, glaucoma, and increased intraocular pressure.

8 USE IN SPECIFIC POPULATIONS

8.1 Pregnancy

Risk Summary

There are no controlled or large-scale epidemiologic studies with Hydrocortisone Butyrate Cream (lipid), 0.1% use in pregnant women, and available data on hydrocortisone butyrate use in pregnant women have not identified a drug-associated risk for major birth defects, miscarriages or adverse maternal or fetal outcomes.

In animal reproduction studies, when administered subcutaneously or topically to pregnant rats, rabbits, and mice, hydrocortisone butyrate induced adverse reproductive and developmental outcomes, including abortion, fetal death, malformation, delayed ossification, decrease in fetal weight, and delay in sexual maturation (see Data). The available data do not allow the calculation of relevant comparisons between the systemic exposure of hydrocortisone butyrate observed in animal studies and the systemic exposure that would be expected in humans after topical use of Hydrocortisone Butyrate Cream (lipid), 0.1%.

The background risk of major birth defects and miscarriage for the indicated population is unknown. All pregnancies have a background risk of birth defect, loss, or other adverse outcomes. In the U.S. general population, the estimated background risk of major birth defects and miscarriage in clinically recognized pregnancies is 2% to 4% and 15% to 20%, respectively.

Data

Animal Data

Systemic embryofetal development studies were conducted in rats and rabbits. Subcutaneous doses of 0.6, 1.8, and 5.4 mg/kg/day hydrocortisone butyrate were administered to pregnant female rats during gestation days 6 - 17. In the presence of maternal toxicity, fetal effects noted at 5.4 mg/kg/day included increased ossification variations and unossified sternebra. No treatment-related embryofetal toxicity or malformation were noted at doses of 5.4 and 1.8 mg/kg/day, respectively.

Subcutaneous doses of 0.1, 0.2, and 0.3 mg/kg/day hydrocortisone butyrate were administered to pregnant female rabbits during gestation days 7 - 20. Increased abortion was noted at 0.3 mg/kg/day. In the absence of maternal toxicity, a dose-dependent decrease in fetal body weight was noted at doses ≥0.1 mg/kg/day. Embryofetal toxicities (reduction in litter size, decreased number of viable fetuses, and increased post-implantation loss) were noted at doses ≥0.2 mg/kg/day. Additional fetal effects included delayed ossification noted at doses ≥0.1 mg/kg/day and increased fetal malformations (primarily skeletal malformations) noted at doses ≥0.2 mg/kg/day. A dose at which no embryofetal toxicity or malformation was observed was not established in this study.

Additional systemic embryofetal development studies were conducted in rats and mice. Subcutaneous doses of 0.1 and 9 mg/kg/day hydrocortisone butyrate were administered to pregnant female rats during gestation days 9 – 15. In the presence of maternal toxicity, an increase in fetal death and fetal resorption and an increase in ossification of caudal vertebrae were noted at 9 mg/kg/day. No treatment-related embryofetal toxicity or malformation was noted at 0.1 mg/kg/day.

Subcutaneous doses of 0.2 and 1 mg/kg/day hydrocortisone butyrate were administered to pregnant female mice during gestation days 7 – 13. In the absence of maternal toxicity, an increased number of cervical ribs and one fetus with clubbed legs were noted at 1 mg/kg/day. No treatment-related embryofetal toxicity or malformation was noted at 1 and 0.2 mg/kg/day.

No topical embryofetal development studies were conducted with hydrocortisone butyrate cream. However, topical embryofetal development studies were conducted in rats and rabbits with a hydrocortisone butyrate ointment formulation. Topical doses of 1% and 10% hydrocortisone butyrate ointment were administered to pregnant female rats during gestation days 6 – 15 or pregnant female rabbits during gestation days 6 -18. A dose-dependent increase in fetal resorption was noted in rabbits and fetal resorptions were noted in rats at the 10% hydrocortisone butyrate ointment dose. No treatment-related embryofetal toxicity was noted at the 1% hydrocortisone butyrate ointment dose in rats. A dose at which no embryofetal toxicity was observed in rabbits after topical administration of hydrocortisone butyrate ointment was not established. No treatment-related malformation was noted at a dose of 10% hydrocortisone butyrate ointment in rats or rabbits.

A peri- and postnatal development study was conducted in rats. Subcutaneous doses of 0.6, 1.8, and 5.4 mg/kg/day hydrocortisone butyrate were administered to pregnant female rats from gestation day 6 to lactation day 20. In the presence of maternal toxicity, a dose-dependent decrease in fetal weight was noted at doses ≥1.8 mg/kg/day). No treatment-related fetal toxicity was noted at 0.6 mg/kg/day. A delay in sexual maturation was noted at 5.4 mg/kg/day. No treatment-related effects on sexual maturation were noted at 1.8 mg/kg/day. No treatment-related effects on behavioral development or subsequent reproductive performance were noted at 5.4 mg/kg/day.

8.2 Lactation

Risk Summary

There are no data on the presence of hydrocortisone in human or animal milk, the effects on the breastfed infant, or the effects on milk production after treatment with Hydrocortisone Butyrate Cream (lipid), 0.1%.

Systemically administered corticosteroids appear in human milk and could suppress growth, interfere with endogenous corticosteroid production, or cause other untoward effects. It is not known whether topical administration of Hydrocortisone Butyrate Cream (lipid), 0.1% could result in sufficient systemic absorption to produce detectable quantities in human milk.

The developmental and health benefits of breastfeeding should be considered along with the mother’s clinical need for Hydrocortisone Butyrate Cream (lipid), 0.1% and any potential adverse effects on the breastfed infant from Hydrocortisone Butyrate Cream (lipid), 0.1% or from the underlying maternal condition.

8.4 Pediatric Use

Corticosteroid-Responsive Dermatoses

The safety and efficacy of Hydrocortisone Butyrate Cream (lipid), 0.1% for relief of the inflammatory and pruritic manifestations of corticosteroid-responsive dermatoses have not been established in pediatric patients.

Atopic Dermatitis

The safety and effectiveness of Hydrocortisone Butyrate Cream (lipid), 0.1% for the topical treatment of mild to moderate atopic dermatitis have been established in pediatric patients 3 months of age and older. Use of Hydrocortisone Butyrate Cream (lipid), 0.1% for this indication is supported by evidence from a multicenter, randomized, vehicle-controlled trial of 264 pediatric subjects 3 months of age and older [see Clinical Studies (14)] .

The safety and efficacy of Hydrocortisone Butyrate Cream (lipid), 0.1% for the topical treatment of mild to moderate atopic dermatitis have not been established in pediatric patients younger than 3 months of age.

Endocrine Adverse Reactions

Eighty-six (86) subjects (between 5 months and 18 years of age) with moderate to severe atopic dermatitis affecting at least 25% of body surface area (BSA) treated with Hydrocortisone Butyrate Cream (lipid), 0.1% 3 times daily for up to 4 weeks were assessed for HPA-axis suppression in two separate studies. Five of the 82 evaluable subjects (6.1%) demonstrated evidence of suppression, where the criterion for defining HPA-axis suppression was a serum cortisol level of ≤18 mcg/dL after cosyntropin stimulation. At the first follow-up visit, approximately 1 month after the conclusion of treatment, cosyntropin stimulation results of all subjects had returned to normal, with the exception of one subject. This last subject recovered adrenal function by 65 days post-treatment [see Clinical Pharmacology (12.2)] .

Because of higher skin-surface-to-body-mass ratios, pediatric patients are at a greater risk than adults of HPA-axis suppression when they are treated with topical corticosteroids [see Warnings and Precautions (5.1)] . They are therefore also at a greater risk of glucocorticosteroid insufficiency after withdrawal of treatment and of Cushing’s syndrome while on treatment. Manifestations of adrenal suppression in pediatric patients include low plasma cortisol levels in response to ACTH stimulation.

Linear growth retardation, delayed weight gain, and intracranial hypertension have also been reported in pediatric patients receiving topical corticosteroids. Manifestations of intracranial hypertension include bulging fontanelles, headaches, and bilateral papilledema.

8.5 Geriatric Use

Clinical trials of Hydrocortisone Butyrate Cream (lipid), 0.1% did not include sufficient numbers of subjects aged 65 years and over to determine whether they respond differently from younger adult subjects.

11 DESCRIPTION

Hydrocortisone Butyrate Cream (lipid), 0.1% contains hydrocortisone butyrate, a non-fluorinated hydrocortisone ester, for topical use. Hydrocortisone butyrate is a corticosteroid.

The chemical name of hydrocortisone butyrate is 11β,17,21-Trihydroxypregn-4-ene-3,20-dione 17-butyrate. It has the following structural formula:

Hydrocortisone butyrate is a white to off-white powder with a molecular weight of 432.56, and a molecular formula of C25H36O6. It is practically insoluble in water, slightly soluble in ether, soluble in methanol, in alcohol, and in acetone, and freely soluble in chloroform.

Each gram of Hydrocortisone Butyrate Cream (lipid), 0.1% contains 1 mg of hydrocortisone butyrate in a white to off-white hydrophilic cream base consisting of anhydrous citric acid, butylparaben, ceteth-20, cetostearyl alcohol, mineral oil, propylparaben, purified water, sodium citrate, and white petrolatum.

12 CLINICAL PHARMACOLOGY

12.1 Mechanism of Action

Corticosteroids play a role in cellular signaling, immune function, inflammation, and protein regulation; however, the precise mechanism of action in atopic dermatitis is unknown.

12.2 Pharmacodynamics

Pharmacodynamics of Hydrocortisone Butyrate Cream (lipid), 0.1% is unknown.

Hypothalamic-Pituitary-Adrenal (HPA) Axis Suppression

Eighty-six (86) subjects (between 5 months and 18 years of age) with moderate to severe atopic dermatitis affecting at least 25% of body surface area (BSA) treated with Hydrocortisone Butyrate Cream (lipid), 0.1% 3 times daily for up to 4 weeks were assessed for HPA-axis suppression in two separate studies. The disease severity (moderate to severe atopic dermatitis) and the dosing regimen (3 times daily) in these HPA-axis trials were different from the subject population (mild to moderate atopic dermatitis) and the dosing regimen (2 times daily) for which Hydrocortisone Butyrate Cream (lipid), 0.1% is indicated. Five of the 82 evaluable subjects (6.1%) demonstrated evidence of suppression, where the criterion for defining HPA-axis suppression was a serum cortisol level of ≤18 mcg/dL after cosyntropin stimulation. Suppressed subjects ranged in age from 5 months to 16 years and, at the time of enrollment, had 25% to 95% BSA involvement. These subjects did not demonstrate any clinical signs or symptoms despite evidence of HPA-axis suppression. At the first follow-up visit, approximately 1 month after the conclusion of treatment, cosyntropin stimulation results of all subjects had returned to normal, with the exception of one subject. This last subject recovered adrenal function by 65 days post-treatment [see Warnings and Precautions (5.1), Use in Specific Populations (8.4)] .

12.3 Pharmacokinetics

The extent of percutaneous absorption of topical corticosteroids is determined by many factors, including the vehicle, the integrity of the epidermal barrier, and the use of occlusive dressings.

Topical corticosteroids can be absorbed through normal intact skin. Inflammation and/or other disease processes in the skin, occlusive dressings, or widespread application may increase percutaneous absorption and increase the risk of HPA-axis suppression.

The vasoconstrictor assay showed that Hydrocortisone Butyrate Cream (lipid), 0.1% had a more pronounced skin blanching effect than Hydrocortisone Butyrate Cream, 0.1%, suggesting greater percutaneous absorption from the former.

Once absorbed through the skin, topical corticosteroids are handled through pharmacokinetic pathways similar to systemically administered corticosteroids.

13 NONCLINICAL TOXICOLOGY

13.1 Carcinogenesis, Mutagenesis, Impairment of Fertility

In a 2-year dermal rat carcinogenicity study with a hydrocortisone butyrate lotion formulation, hydrocortisone butyrate was administered to Sprague-Dawley rats at topical doses of 0.05, 0.15, and 0.3 mg/kg/day in males and 0.1, 0.25, and 0.5 mg/kg/day in females (0.1% lotion). No drug-related tumors were noted in this study up to the highest doses evaluated in this study of 0.3 mg/kg/day in males and 0.5 mg/kg/day in females.

Hydrocortisone butyrate revealed no evidence of mutagenic or clastogenic potential based on the results of two in vitro genotoxicity tests (Ames test and L5178Y/TK+/-mouse lymphoma assay) and one in vivo genotoxicity test (mouse micronucleus assay).

No evidence of impairment of fertility or effect on mating performance was observed in a fertility and general reproductive performance study conducted in male and female rats at subcutaneous doses up to 1.8 mg/kg/day. Mild effects on maternal animals, such as reduced food consumption and a subsequent reduction in body weight gain, were seen at doses ≥0.6 mg/kg/day.

14 CLINICAL STUDIES

In a multicenter, randomized, vehicle-controlled trial of 264 pediatric subjects 3 months age and older with mild to moderate atopic dermatitis, Hydrocortisone Butyrate Cream (lipid), 0.1% or vehicle was applied twice daily for up to 4 weeks. Treatment success was assessed at Day 29 (after 28 days of treatment) and was defined as the proportion of subjects who achieved both “clear” or “almost clear” and at least a 2-grade improvement from baseline on a 5-point Physician’s Global Assessment (PGA) scale. The trial results are shown in Table 2.

Table 2. Efficacy Results at Day 29 in Pediatric Subjects 3 Months of Age and Older with Mild to Moderate Atopic Dermatitis
 |  | Hydrocortisone Butyrate Cream (lipid), 0.1% (n=131) | Vehicle (n=133)
Number (%) of successes |  | 82 (63%) | 37 (28%)

16 HOW SUPPLIED/STORAGE AND HANDLING

How Supplied

Hydrocortisone Butyrate Cream (lipid), 0.1% is white to off-white in color, and supplied in:

- tubes of 45 g: NDC 68682-384-45
- tubes of 60 g: NDC 68682-384-60

Storage and Handling

Store at 25°C (77°F); excursions permitted to 15° to 30°C (59° to 86°F) [see USP Controlled Room Temperature]. Protect from freezing.

17 PATIENT COUNSELING INFORMATION

Patients using Hydrocortisone Butyrate Cream (lipid), 0.1% should receive the following information and instructions:

Administration Instructions [see Dosage and Administration (2)]

- Corticosteroid-Responsive Dermatoses:
- Instruct patients to apply a thin layer to the affected skin areas 2 or 3 times daily for corticosteroid-responsive dermatoses in adults and rub in gently.
- Atopic Dermatitis:
- Instruct patients to apply a thin layer to the affected skin areas 2 times daily for atopic dermatitis in patients 3 months of age or older and rub in gently.
- Advise patients to discontinue Hydrocortisone Butyrate Cream (lipid), 0.1% when control is achieved.
- Instruct patients to contact their healthcare provider if no improvement is seen within 2 weeks.
- Advise patients to not [see Warnings and Precautions (5.1)]:
- Bandage, otherwise cover, or wrap the affected skin area so as to be occlusive unless directed by their healthcare provider.
- Use Hydrocortisone Butyrate Cream (lipid), 0.1% in the diaper area, as diapers or plastic pants may constitute occlusive dressings.
- Use Hydrocortisone Butyrate Cream (lipid), 0.1% on the face, underarms, or groin areas unless directed by their healthcare provider.

Endocrine System Adverse Reactions

Advise patients to not use other corticosteroid-containing products while using Hydrocortisone Butyrate Cream (lipid), 0.1% without first consulting their healthcare provider [see Warnings and Precautions (5.1)] .

Ophthalmic Adverse Reactions

Advise patients to avoid contact with the eyes. Instruct patients to report any visual symptoms to their healthcare providers [see Warnings and Precautions (5.2)] .

Lactation

Advise patients that are breastfeeding to use Hydrocortisone Butyrate Cream (lipid), 0.1% on the smallest area of skin and for the shortest duration possible while breastfeeding. Advise patients to wash off prior to breastfeeding any Hydrocortisone Butyrate Cream (lipid), 0.1% that has been applied to the areas at risk for direct infant contact [see Use in Specific Populations (8.2)] .

Distributed by:

Oceanside Pharmaceuticals, a division of

Bausch Health US, LLC

Bridgewater, NJ 08807 USA

Manufactured by:

Ferndale Laboratories, Inc.

Ferndale, MI 48220 USA

© 2024 Bausch Health Companies Inc. or its affiliates

9438002

Package/Label Display Panel: Hydrocortisone Butyrate Cream (lipid), 0.1% - 60 g Carton

NDC68682-384-60

Rx only

HYDROCORTISONE BUTYRATE CREAM (lipid)
0.1%

For topical use only
Net Wt. 60 g

OCEANSIDE
PHARMACEUTICALS